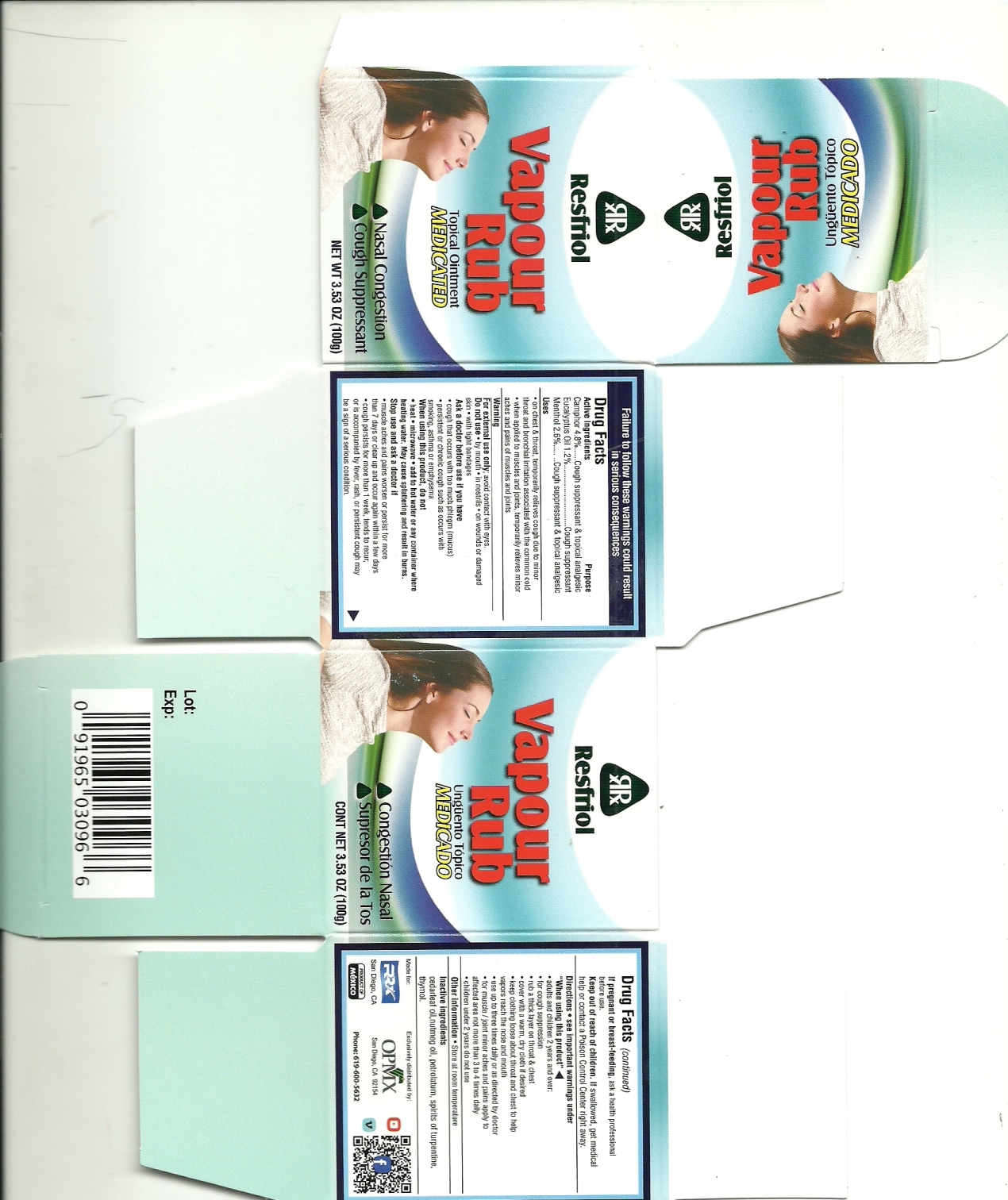 DRUG LABEL: VAPOUR RUB
NDC: 69728-0030 | Form: OINTMENT
Manufacturer: PROSANA DISTRIBUCIONES, S.A. DE C.V.
Category: otc | Type: HUMAN OTC DRUG LABEL
Date: 20170501

ACTIVE INGREDIENTS: EUCALYPTUS OIL 1.2 g/100 g; CAMPHOR (SYNTHETIC) 4.8 g/100 g; MENTHOL 2.6 g/100 g
INACTIVE INGREDIENTS: THYMOL 1.2 g/100 g; PETROLATUM 87.3 g/100 g; CEDAR LEAF OIL 1.2 g/100 g; NUTMEG OIL 1.2 g/100 g; TURPENTINE OIL 0.5 g/100 g

VAPOUR RUB 100g

Active Ingredients Purpose

Camphor 4.8 % Cough Suppresant & Topical Analgesic

Eucalyptus Oil 1.2% Cough Suppresant

Menthol 2.6% Cough Suppresant and Topical Analgesic

Uses

-on chest and throat, temporarily relieves cough due to minor throat and bronchial irritation associated with the common cold. when applied to muscles and joints , temporarily relieves minor aches and pains of muscles and joints

Store

Other Information-Store at room temperature

Inactive ingredients

cedarleaf oil, nutmeg oil, spirits of turpentine, thymol

Directions-See important warnings under "When Using This Product"

For external use only; avoid contact with eyes

Do not use

-by mouth

-in nostrils

-on wounds

or damaged skin

-with light bandages

Ask a doctor before use if you have

-cough that occurs with too much phlegm

-persistant or chronic cough, such as occurs with smoking, asthma or emphysema

When using this product do not:

-heat-microwave-add to hot water or any container where heating water. May cause splattering and result in burns.

Stop use

Stop use and ask a doctor if

-muscle aches and pains worsen or persist for more than 7 days or clear up and occur again after a few days

-cough persists for more than 1 week, tends to recur, or is accompanied by fever, rash, or persistent cough may be a sign of a serious condition

If pregnant

If pregnant or breastfeeding ask a health professional before use

Keep out

Keep out of reach of children. If swallowed, get medical help or contact a Poison Control Center right away.

Directions

Directions-see important warnings under "when using this product"

-adults and children 2 years and over

-for cough suppression

-rub a thick layer on throat and chest

-cover with a warm cloth if desired

-keep clothing loose around throat and chest to help vapors reach the nose and mucus

-use up to three times a day or as directed by a doctor

-for muscle/joint aches and pains apply to affected area no more than 3 to 4 times daily

-children under 2 years do not use

If pregnant

If pregnant or breast feeding, ask a health professional before use

Children

Keep out of reach of children. If swallowed, get medical help or contact a Poison Center

Warning

Failure to follow these warnings could result in serious consequences

For external use only, avoid contact with eyes

Do not use-by mouth-in nostrils-on wounds of damaged skin-with tight bandages

Ask a doctor before use if you have

-cough that occurs with too much phlegm (mucus)

-persistent or chronic cough such as occurs with smoking, asthma or emphysema

When using this product, do not

-heat-microwave-add to hot water or any container where heating water. May cause splattering and result in burns

Stop use and ask a doctor if

-musche aches and pains worsen or persist for more than 7 days or clear up and accur again after a few days

-cough persit for more than 1 week, tends to recur, or is accompanied by fever, rash, or persistent cough may be a sign of a serious condition

Principal display 100 g

RESFRIOL

VAPOUR RUB

TOPICAL OINTMENT -MEDICATED

-Nasal Congestion

-Cough Suppresant

NET WT. 3.53 OZ (100g)